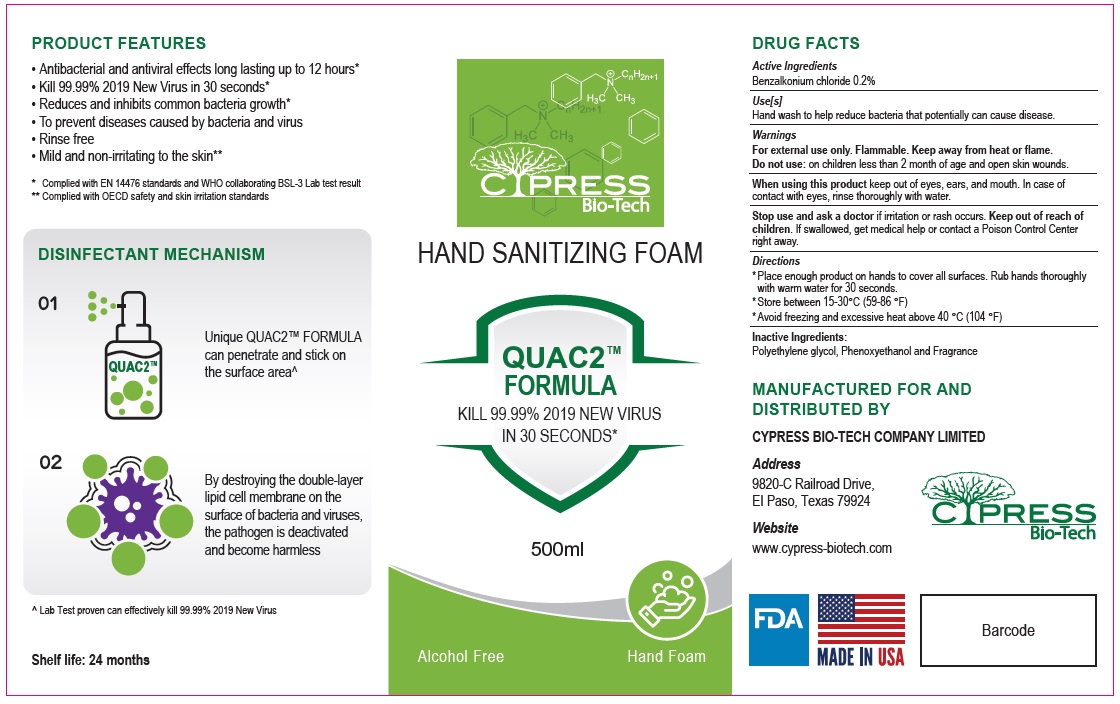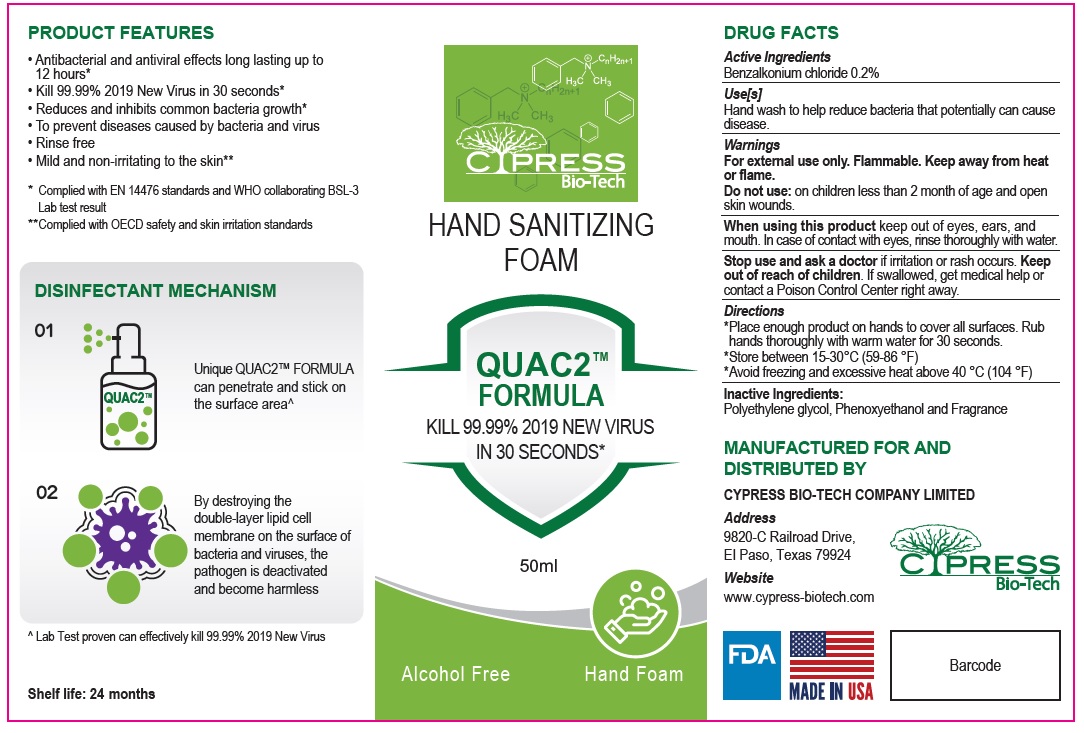 DRUG LABEL: CYPRESS Bio-Tech Hand Sanitizing Foam
NDC: 78804-213 | Form: LIQUID
Manufacturer: Allure Chemicals LP
Category: otc | Type: HUMAN OTC DRUG LABEL
Date: 20210507

ACTIVE INGREDIENTS: BENZALKONIUM CHLORIDE 0.2 g/100 mL
INACTIVE INGREDIENTS: POLYETHYLENE GLYCOL 400; PHENOXYETHANOL

CYPRESS Bio-Tech HAND SANITIZING FOAM

Active Ingredients

Benzalkonium chloride 0.2%

Purpose

Antibacterial

Use[s]

Hand wash to help bacteria that potentially can cause disease.

Warnings

For external use only. Flammable. Keep away from heat or flame.

Do not use: on children less than 2 month of age and open skin wounds.

When using this product keep out of eyes, ears, and mouth. In case of contact with eyes, rinse thoroughly with water.

Stop use and ask a doctor if irritation or rash occurs.

Keep out of reach of children. If swallowed, get medical help or contact a Poison Control Center right away.

Directions

* Place enough product on hands to cover all surfaces. Rub hands thoroughly with warm water for 30 seconds.

* Store between 15-30°C (59-86 °F)

* Avoid freezing and excessive heat above 40 °C (104 °F)

Inactive Ingredients:

Polyethylene glycol, Phenoxyethanol and Fragrance

QUAC2™

FORMULA

KILL 99.99% 2019 NEW VIRUS IN 30 SECONDS*

Alcohol Free

Hand Foam

PRODUCT FEATURES

• Antibacterial and antiviral effects long lasting up to 12 hours*
• Kill 99.99% 2019 New Virus in 30 seconds*
• Reduces and inhibits common bacteria growth*
• To prevent diseases caused by bacteria and virus
• Rinse free
• Mild and non-irritating to the skin**

* Complied with EN 14476 standards and WHO collaborating BSL-3 Lab test result
**Complied with OECD safety and skin irritation standards

DISINFECTANT MECHANISM

01 Unique QUAC2™ FORMULA can penetrate and stick on the surface area^

02 By destroying the double-layer lipid cell membrane on the surface of bacteria and viruses, the pathogen is deactivated and become harmless

^ Lab Test proven can effectively kill 99.99% 2019 New Virus

Shelf life: 24 months

MANUFACTURED FOR AND DISTRIBUTED BY

CYPRESS BIO-TECH COMPANY LIMITED

Address

9820-C Railroad Drive,
El Paso, Texas 79924

Website

www.cypress-biotech.com

MADE IN USA